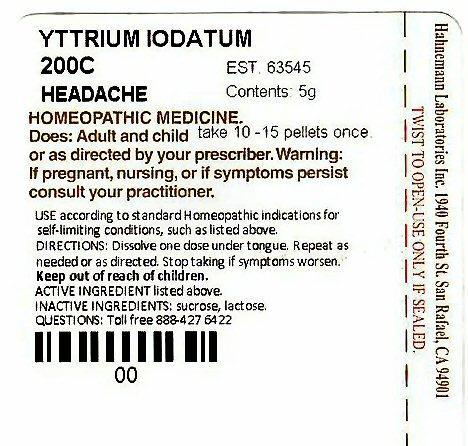 DRUG LABEL: HAHNEMANN HEADACHE
NDC: 63545-637 | Form: PELLET
Manufacturer: Hahnemann Laboratories, Inc. dba Alpine Pharmaceuticals
Category: homeopathic | Type: HUMAN OTC DRUG LABEL
Date: 20120114

ACTIVE INGREDIENTS: YTTRIUM IODIDE 200 [hp_C]/1 1
INACTIVE INGREDIENTS: SUCROSE; LACTOSE

Active Ingredients

ACTIVE INGREDIENT listed above

YTTRIUM IODATUM

Purpose

HEADACHE

Keep Out Of Reach Of Children

Use

USE according to standard Homeopathic indications for self-limiting conditions, such as listed above. HEADACHE

Warnings

Warning: If pregnant, or nursing, or if symptoms persist consult your practitioner.

Directions

DIRECTIONS: Dissolve one dose under tongue. Repeat as needed or as directed. Stop taking if symptoms worsen.

DOSE: Adults and children take 10 - 15 pellets once or as directed by your prescriber.

Inactive Ingredient

INACTIVE INGREDIENTS: sucrose, lascose.

Package Label

YTTRIUM IODATUM 200C HEADACHE EST. 63545 Contains 5 g

HOMEOPATHIC MEDICINE

Hahnemann Laboratories Inc. 1940 Fourth St. San Rafael, CA 94901

TWIST TO OPEN-USE ONLY IF SEALED

Questions: Toll free 888-427-6422